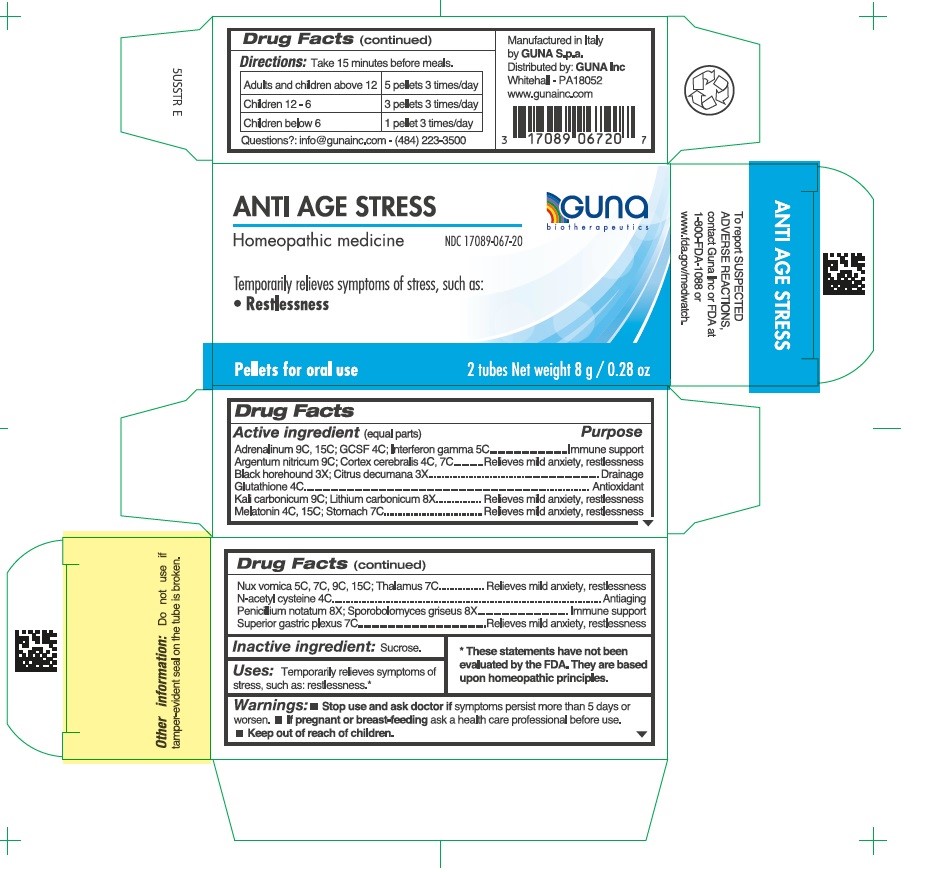 DRUG LABEL: ANTI AGE STRESS
NDC: 17089-067 | Form: PELLET
Manufacturer: Guna spa
Category: homeopathic | Type: HUMAN OTC DRUG LABEL
Date: 20231102

ACTIVE INGREDIENTS: MELATONIN 15 [hp_C]/4 g; ACETYLCYSTEINE 4 [hp_C]/4 g; STRYCHNOS NUX-VOMICA SEED 5 [hp_C]/4 g; PENICILLIUM GLABRUM 8 [hp_X]/4 g; RHODOTORULA RUBRA 8 [hp_X]/4 g; SUS SCROFA STOMACH 7 [hp_C]/4 g; SUS SCROFA SUPERIOR GASTRIC PLEXUS 7 [hp_C]/4 g; SUS SCROFA THALAMUS 7 [hp_C]/4 g; EPINEPHRINE 9 [hp_C]/4 g; SILVER NITRATE 9 [hp_C]/4 g; BALLOTA FOETIDA 3 [hp_X]/4 g; PUMMELO 3 [hp_X]/4 g; SUS SCROFA CEREBRAL CORTEX 4 [hp_C]/4 g; POTASSIUM CARBONATE 9 [hp_C]/4 g; LENOGRASTIM 4 [hp_C]/4 g; GLUTATHIONE 4 [hp_C]/4 g; INTERFERON GAMMA-1B 5 [hp_C]/4 g; LITHIUM CARBONATE 8 [hp_X]/4 g
INACTIVE INGREDIENTS: SUCROSE 3.5 g/4 g

ANTI AGE STRESS

ACTIVE INGREDIENT

Adrenalinum 9C, 15C, GCSF 4C, Interferon gamma 5C.......................Immune support

Argentum nitricum 9C, Cortex cerebralis 4C, 7C....................................Relieves mild anxiety, restlessness

Black horehound 3X, Citrus decumana 3X.............................................Drainage

Glutathione 4C........................................................................................Antioxidant

Kali carbonicum 9C, Lithium carbonicum 8X..........................................Relieves mild anxiety, restlessness

Melatonin 4C, 15C, Stomach 7C............................................................Relieves mild anxiety, restlessness

Nux vomica 5C, 7C, 9C, 15, Thalamus 7C.............................................Relieves mild anxiety, restlessness

N-acetyl cysteine 4C...............................................................................Antiaging

Penicillium notatum 8X, Sporobolomyces griseus 8X.............................Immune support

Superior gastric plexus 7C......................................................................Relieves mild anxiety, restlessness

PURPOSE

Temporarily relieves symptoms of stress, such as:

- Restlessness

- Stop use and ask doctor if symptoms persist more than 5 days or worsen.
- If pregnant or breast-feeding ask a health care professional before use.
- Keep out of reach of children.

PREGNANCY OR BREAST FEEDING

If pregnant or breast-feeding ask a health professional before use.

Keep out of reach of children

DOSAGE AND ADMINISTRATION

Adults and children 12 years and older 5 pellets 3 times per day
Children between 12 years and 6 years of age 3 pellets 3 times per day
Children under 6 years 1 pellet 3 times per day to be dissolved into a little water

Questions?: info@gunainc.com
tel. (484) 223-3500

Inactive ingredient: Sucrose.

DIRECTIONS

- Turn tube upside down and rotate cap to release pellets into cap.
- Unscrew cap and without touching pellets tip them into the mouth under the tongue.
- Allow to dissolve
- Take 15 minutes before meals.